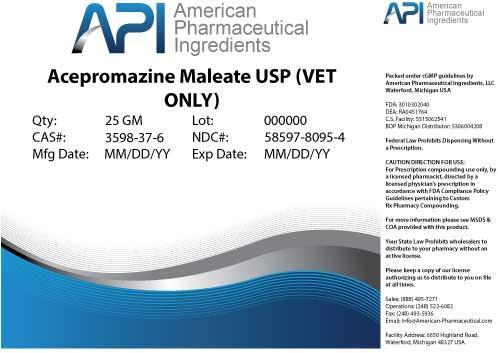 DRUG LABEL: Acepromazine Maleate
NDC: 58597-8095 | Form: POWDER
Manufacturer: AMERICAN PHARMACEUTICAL INGREDIENTS LLC
Category: other | Type: BULK INGREDIENT
Date: 20140416

ACTIVE INGREDIENTS: Acepromazine Maleate 1 g/1 g

Acepromazine Maleate